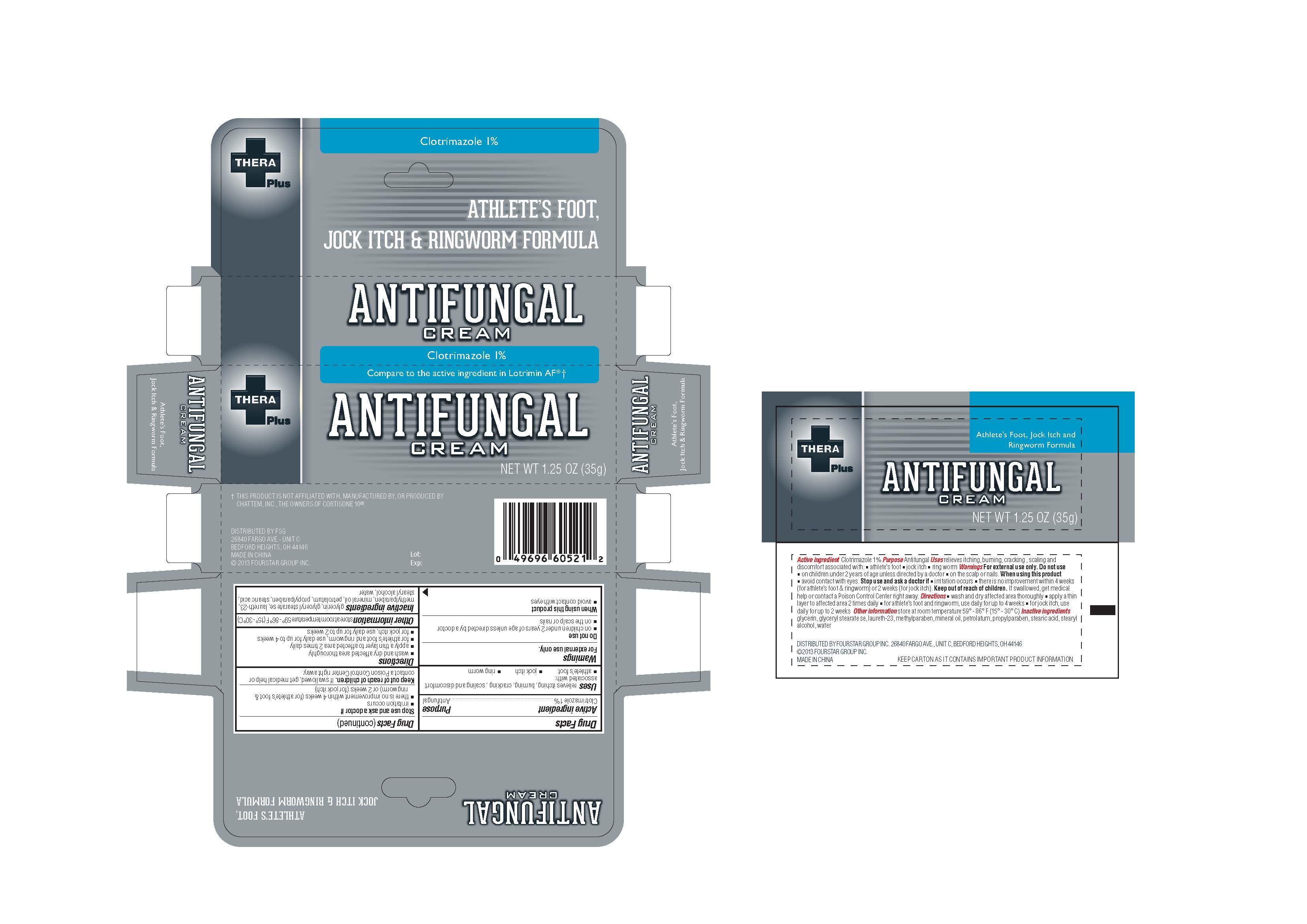 DRUG LABEL: TheraPlus				
NDC: 55621-003 | Form: CREAM
Manufacturer: Zhejiang Jingwei Pharmaceutical Co., Ltd.
Category: otc | Type: HUMAN OTC DRUG LABEL
Date: 20231027

ACTIVE INGREDIENTS: CLOTRIMAZOLE 1 g/100 g
INACTIVE INGREDIENTS: GLYCERIN; GLYCERYL STEARATE SE; LAURETH-23; METHYLPARABEN; MINERAL OIL; PETROLATUM; PROPYLPARABEN; STEARIC ACID; STEARYL ALCOHOL; WATER

Drug Facts

INACTIVE INGREDIENT

glycerin, glyceryl stearate se, laureth-23, methylparaben, mineral oil, prophylparaben, stearic acid, stearyl alcohol, water Inactive Ingredients

Active Ingredient

Clotrimazole 1%

Warnings

For external use only

Do not use

on children under 2 years of age unless directed by a doctor

on the scalp or nails

When using this product

avoid contact with eyes

Purpose

Antifungal

KEEP OUT OF REACH OF CHILDREN

. If swallowed, get medical help or contact a Poison Control Center right away Keep out of reach of children

INDICATIONS AND USAGE

relieves itching, burning, cracking, scaling and discomfort associated with: Uses

-athletes foot -jock itch -ring worm

Directions

-wash and dry affected area thoroughly

-apply a thin layer to affected area 2 times daily

-for athlete's foot and ringworm, use daily for up to 4 weeks

-for jock itch, use daily for up to 2 weeks